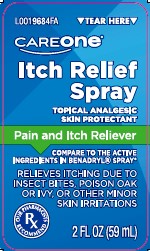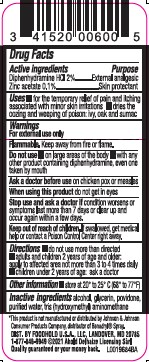 DRUG LABEL: Itch Relief
NDC: 72476-295 | Form: SPRAY
Manufacturer: Retail Business Services, LLC
Category: otc | Type: HUMAN OTC DRUG LABEL
Date: 20260206

ACTIVE INGREDIENTS: DIPHENHYDRAMINE HYDROCHLORIDE 20 mg/1 mL; ZINC ACETATE 1 mg/1 mL
INACTIVE INGREDIENTS: ALCOHOL; GLYCERIN; POVIDONE; WATER; TROMETHAMINE

Care One 295.000/295AB
Itch Relief Spray

Active ingredients

Diphenhydramine HCl 2%
Zinc Acetate 0.1%

Purpose

External analgesic
Skin protectant

Uses

- for the temporary relief of pain and itching associated with minor skin irratations
- dries the oozing and weeping of poison: ivy, oak and sumac

Warnings

For external use only

Flammable. Keep away from fire of flame.

Do not use

- on large areas of the body
- with any other product containing diphenhydramine, even one taken by mouth

Ask a doctor before use

on chicken pox or measles

When using this product

do not get into eyes

Stop use and ask a doctor if

condition worsens or symptoms last more than 7 days or clear up and occur again within a few days.

Keep out of reach of children.

If swallowed, get medical help or contact a Poison Control Center right away.

Directions

•do not use more than directed
•adults and children 2 years of age and older: apply to affected area not more than 3 to 4 times daily
•children under 2 years of age: ask a doctor

Other information

• store at 20⁰ to 25⁰C (68⁰ to 77⁰F)

Inactive ingredients

alcohol, glycerin, povidone, purified water, tris (hydroxymethyl) aminomethane

Disclaimer

*This product is not manufactured or distributed by Johnson & Johnson Consumer Products Company, distributor of Benadryl®Spray.

ADVERSE REACTION

DIST. BY FOODHOLD U.S.A., LLC

LANDOVER, MD 20785

1-877-846-9949 ©2021 Ahold Delhaize Licensing Sari

Quilty guaranteed or money back.

principal display panel

TEAR HERE

CAREONE®

Itch Relief Spray

TOPICAL ANALGESIC

SKIN PROTECTANT

Pain and Itch Reliever

COMPARE TO THE ACTIVE INGREDIENTS IN BENADRYL®SPRAY*

RELIEVES ITCHING DUE TO INSECT BITES, POISON OAK OR IVY, OR OTHER MINOR SKIN IRRITATIONS

OUR PHARMACISTS RECOMMEND

2 FL OZ (59 mL)